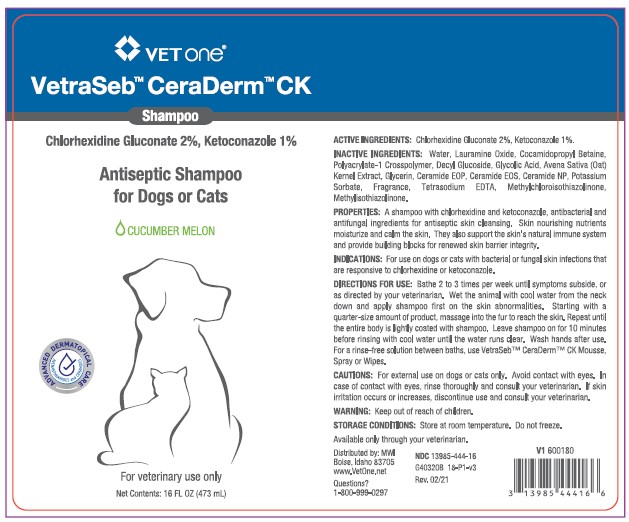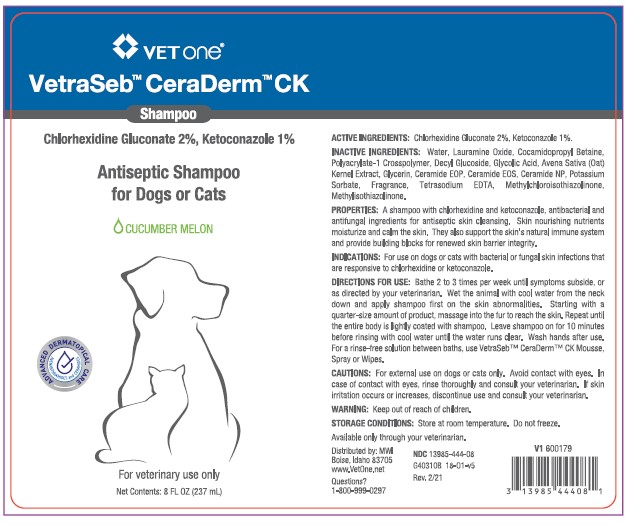 DRUG LABEL: VetraSeb CeraDerm
NDC: 13985-444 | Form: SHAMPOO
Manufacturer: MWI/VETONE
Category: animal | Type: OTC ANIMAL DRUG LABEL
Date: 20210407

ACTIVE INGREDIENTS: CHLORHEXIDINE GLUCONATE 20 mg/1 mL; KETOCONAZOLE 10 mg/1 mL
INACTIVE INGREDIENTS: WATER; LAURAMINE OXIDE; COCAMIDOPROPYL BETAINE; CARBOMER HOMOPOLYMER, UNSPECIFIED TYPE; DECYL GLUCOSIDE; GLYCOLIC ACID; AVENANTHRAMIDES; GLYCERIN; CERAMIDE 1; CERAMIDE EOS; CERAMIDE NP; POTASSIUM SORBATE; EDETATE SODIUM; METHYLCHLOROISOTHIAZOLINONE; METHYLISOTHIAZOLINONE

DESCRIPTION

VetraSeb™ CeraDerm™ CK

Shampoo

ACTIVE INGREDIENTS: Chlorhexidine Gluconate 2%, Ketoconazole 1%.

INACTIVE INGREDIENTS: Water, Lauramine Oxide, Cocamidopropyl Betaine, Polyacrylate-1 Crosspolymer, Decyl Glucoside, Glycolic Acid, Avena Sativa (Oat) Kernel Extract, Glycerin, Ceramide EOP, Ceramide EOS, Ceramide NP, Potassium Sorbate, Fragrance, Tetrasodium EDTA, Methylchloroisothiazolinone, Methylisothiazolinone.

PROPERTIES: A shampoo with chlorhexidine and ketoconazole, antibacterial and antifungal ingredients for antiseptic skin cleansing. Skin nourishing nutrients moisturize and calm the skin. They also support the skin’s natural immune system and provide building blocks for renewed skin barrier integrity.

INDICATIONS AND USAGE

INDICATIONS: For use on dogs and cats with bacterial or fungal skin infections that are responsive to chlorhexidine gluconate and ketoconazole.

DIRECTIONS FOR USE: Bathe 2 to 3 times per week until symptoms subside or as directed by your veterinarian. Wet the animal with cool water from the neck down and apply shampoo first on the skin abnormalities. Starting with a quarter-size amount of product, massage into the fur to reach the skin. Repeat until the entire body is lightly coated with shampoo. Leave shampoo on for 10 minutes before rinsing with cool water until the water runs clear. Wash hands after use. For a rinse-free solution between baths, use VetraSeb™ CeraDerm™ CK Mousse, Spray or Wipes.

WARNINGS AND PRECAUTIONS

CAUTIONS: For external use on dogs or cats only. Avoid contact with eyes. In case of contact with eyes, rinse thoroughly and consult your veterinarian. If skin irritation occurs or increases, discontinue use and consult your veterinarian.

WARNING: Keep out of reach of children.

STORAGE AND HANDLING

STORAGE CONDITIONS: Store at room temperature. Do not freeze.

Available only through your veterinarian.

Distributed by: MWI

Boise, Idaho 83705

www.VetOne.net

QUESTIONS?

1-800-999-0297

PRINCIPAL DISPLAY PANEL - 8 OUNCE (237 mL) Bottle

VetOne®

VetraSeb™ CeraDerm™ CK

Shampoo

Chlorhexidine Gluconate 2%, Ketoconazole 1%

Antiseptic Shampoo for Dogs or Cats

CUCUMBER MELON

For veterinary use only

Net Contents: 8 FL. OZ. (237 mL)

PRINCIPAL DISPLAY PANEL - 16 OUNCE (473 mL) Bottle

VetOne®

VetraSeb™ CeraDerm™ CK

Shampoo

Chlorhexidine Gluconate 2%, Ketoconazole 1%

Antiseptic Shampoo for Dogs or Cats

CUCUMBER MELON

For veterinary use only

16 FL.OZ. (473 mL)